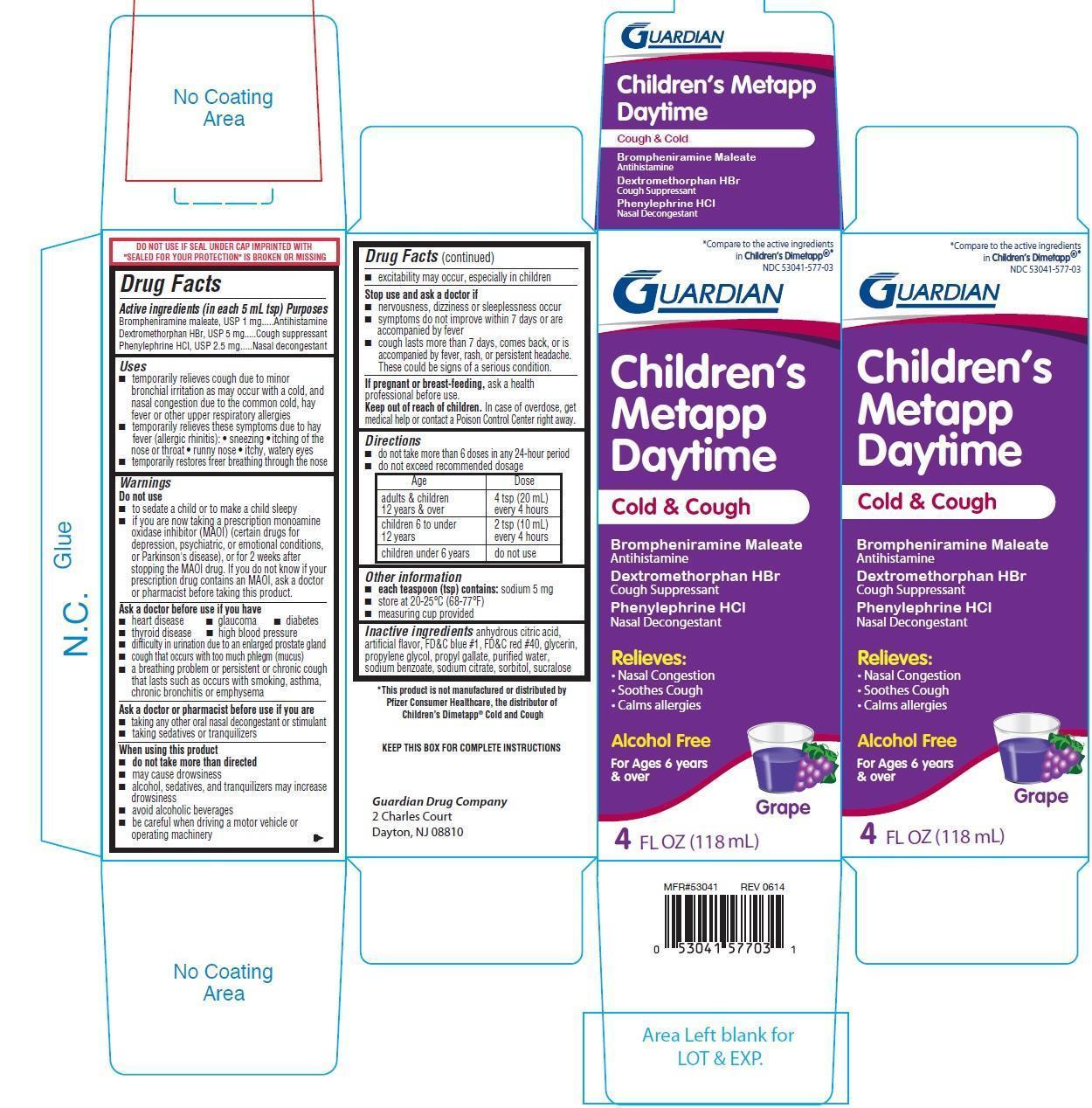 DRUG LABEL: Childrens Metapp Daytime
NDC: 53041-577 | Form: LIQUID
Manufacturer: Guardian Drug Company
Category: otc | Type: HUMAN OTC DRUG LABEL
Date: 20241218

ACTIVE INGREDIENTS: BROMPHENIRAMINE MALEATE 1 mg/5 mL; DEXTROMETHORPHAN HYDROBROMIDE 5 mg/5 mL; PHENYLEPHRINE HYDROCHLORIDE 2.5 mg/5 mL
INACTIVE INGREDIENTS: ANHYDROUS CITRIC ACID; FD&C BLUE NO. 1; FD&C RED NO. 40; GLYCERIN; PROPYLENE GLYCOL; PROPYL GALLATE; WATER; SODIUM BENZOATE; SODIUM CITRATE; SORBITOL; SUCRALOSE

Childrens Metapp Daytime Cold and Cough

Active ingredients (in each 5 mL tsp)

Brompheniramine maleate 1 mg
Dextromethorphan HBr 5 mg

Phenylephrine HCl 2.5 mg

Purposes

Antihistamine

Cough suppressant

Nasal decongestant

Uses

- temporarily relieves cough due to minor bronchial irritation as may occur with a cold, and nasal congestion due to the common cold, hay fever or other upper respiratory allergies
- temporarily relieves these symptoms due to hay fever (allergic rhinitis):
- sneezing
- itching of the nose or throat
- runny nose
- itchy, watery eyes
- temporarily restores freer breathing through the nose

Warnings

Do not use

- to sedate a child or to make a child sleepy
- if you are now taking a prescription monoamine oxidase inhibitor (MAOI)(certain drugs for depression, psychiatric, or emotional conditions, or parkinsons disease), or for 2 weeks after stopping the MAOI drug. If you do not know if your prescription drug contains an MAOI, ask a doctor or pharmacist before taking this product.

Ask a doctor before use if you have

- heart disease
- glaucoma
- diabetes
- thyroid disease
- high blood pressure
- difficulty in urination due to an enlarged prostate gland
- cough that occurs with too much phlegm (mucus)
- a breathing problem or persistent or chronic cough that lasts such as occurs with smoking asthma, chronic bronchitis or emphysema

Ask a doctor or pharmacist before use if you are

- taking any other oral nasal decongestant or stimulant
- taking sedatives or tranquilizers

when using this product

- do not take more than directed
- may cause drowsiness
- alcohol, sedatives, and tranquilizers may increase drowsiness
- avoid alcohol beverages
- be careful when driving a motor vehicle or operating mahcinery
- excitability may occur, especially in children

Stop use and ask a doctor if

- nervousness, dizziness or sleeplessness occur
- symptoms do not improve within 7 days or are accompanied by fever
- cough lasts more than 7 days, comes back, or is accompanied by fever, rash, or persistent headache. These could be signs of a serious condition.

If pregnant or breast feeding,

ask a health professional before use.

Keep out of reach of children. In case of overdose, get medical help or contact a Poison Control Center right away.

Directions

- do not take more than 6 doses in any 24-hour period
- do not exceed recommended dosage

Age | Dose
adults and children 12 years and over | 4 tsp (20 mL) every 4 hours
children 6 to under 12 years | 2 tsp (10 mL) every 4 hours
children under 6 years | do not use

Other information

- each teaspoon (tsp) contains: sodium 5 mg
- store at 20-25oC (68-77oF)
- measuring cup provided

Inactive ingredients

anhydrous citric acid, artificial flavor, FD&C BLUE #1, FD&C red 40, glycerin, propylene glycol, propyl gallate, purified water, sodium benzoate, sodium citrate, sorbitol, sucralose

PDP

Compare to the active ingredients in Childrens Dimetapp

Childrens Metapp Daytime

Cold & Cough

Brompheniramine Maleate

Antihistamine

Dextromethorphan HBr

Cough Suppressant

Phenylephrine HCl

Nasal Decongestant

Relieves:

- Nassal Congestion
- Soothes Cough
- Calms allergies

Alcohol Free

For ages 6 years and over

Grape

4 FL OZ (118 mL)